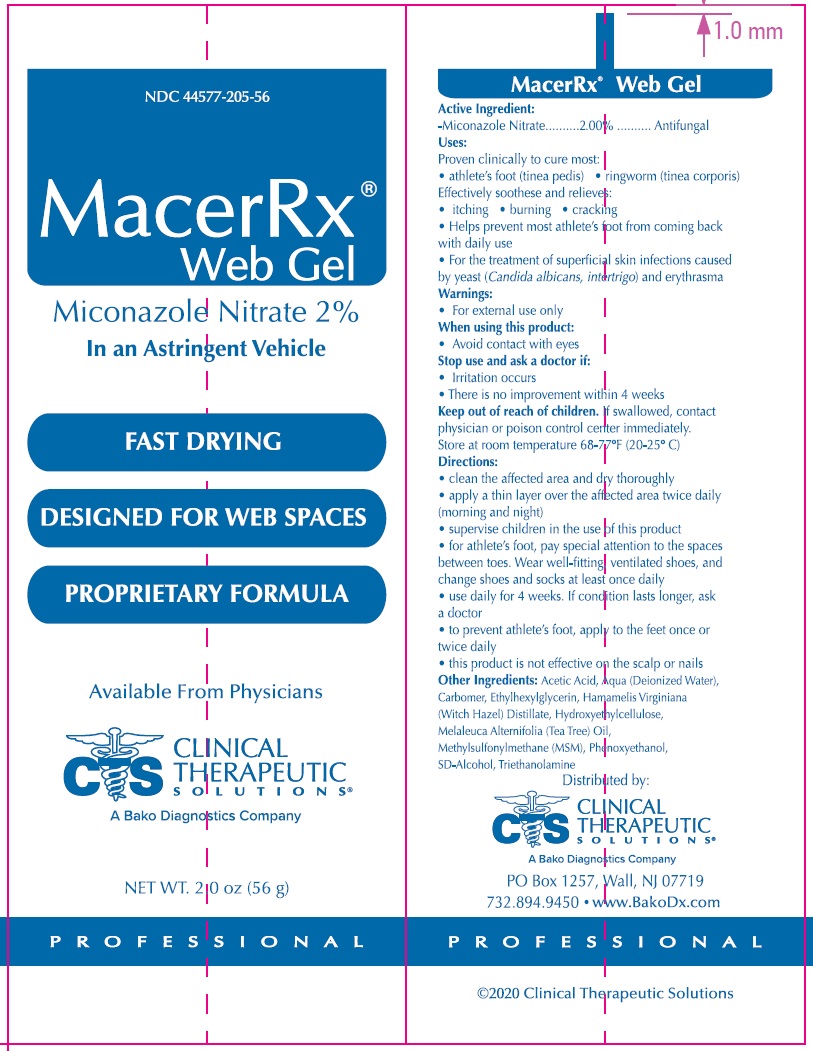 DRUG LABEL: MacerRx Web
NDC: 44577-205 | Form: CREAM
Manufacturer: Clinical Therapeutic Solutions
Category: otc | Type: HUMAN OTC DRUG LABEL
Date: 20231105

ACTIVE INGREDIENTS: MICONAZOLE NITRATE 2 g/100 g
INACTIVE INGREDIENTS: ACETIC ACID; WATER; CARBOMER HOMOPOLYMER, UNSPECIFIED TYPE; ETHYLHEXYLGLYCERIN; WITCH HAZEL; HYDROXYETHYL CELLULOSE, UNSPECIFIED; TEA TREE OIL; DIMETHYL SULFONE; PHENOXYETHANOL; TROLAMINE

MacerRx Web Gel

Active Ingredient:

-Miconazole Nitrate 2.00%

PURPOSE

Antifungal

Uses:

Proven clinically to cure most:

- athlete’s foot (tinea pedis)
- ringworm (tinea corporis) Effectively soothese and relieves:
- itching
- burning
- cracking
- Helps prevent most athlete’s foot from coming back with daily use
- For the treatment of superficial skin infections caused by yeast (Candida albicans, intertrigo) and erythrasma

Warnings:

- For external use only

When using this product:

- Avoid contact with eyes

Stop use and ask a doctor if:

- Irritation occurs
- There is no improvement within 4 weeks

Keep out of reach of children.

If swallowed, contact physician or poison control center immediately.

Store at room

temperature 68-77ºF (20-25º C)

Directions:

- clean the affected area and dry thoroughly
- apply a thin layer over the affected area twice daily (morning and night)
- supervise children in the use of this product
- for athlete’s foot, pay special attention to the spaces between toes. Wear well-fitting, ventilated shoes, and change shoes and socks at least once daily
- use daily for 4 weeks. If condition lasts longer, ask a doctor
- to prevent athlete’s foot, apply to the feet once or twice daily
- this product is not effective on the scalp or nails

Other Ingredients:

Acetic Acid, Aqua (Deionized Water), Carbomer, Ethylhexylglycerin, Hamamelis Virginiana (Witch Hazel) Distillate, Hydroxyethylcellulose, Melaleuca Alternifolia (Tea Tree Oil), Methylsulfonylmethane (MSM), Phenoxyethanol, SD-Alcohol, Triethanolamine